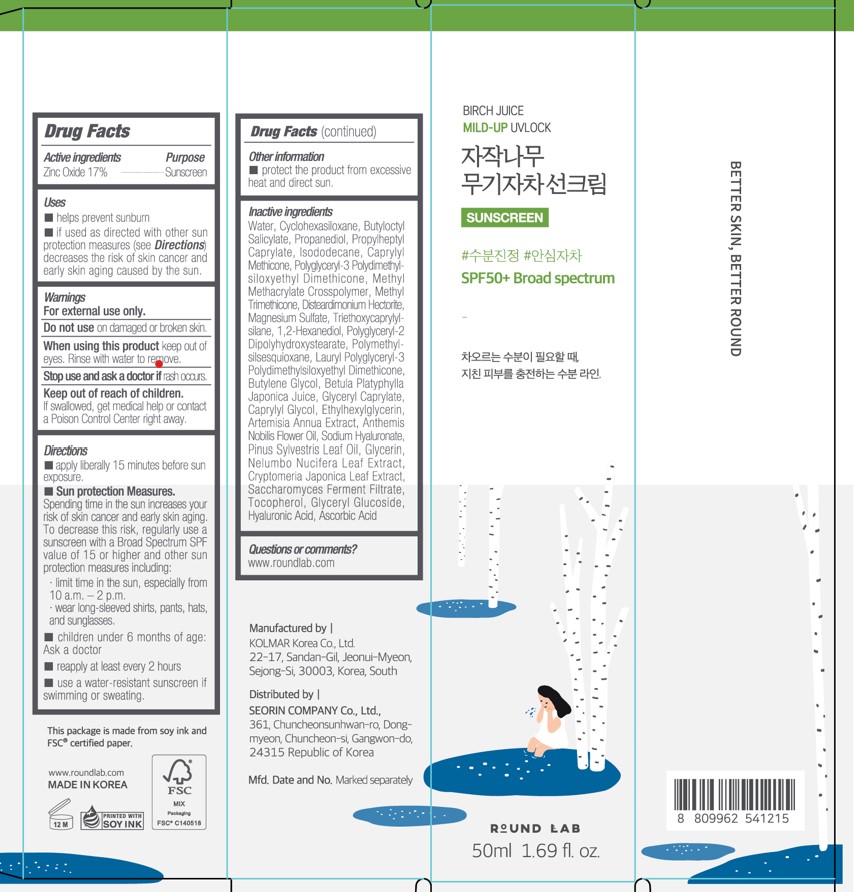 DRUG LABEL: Round Lab Birch Juice Mild-Up UVLOCK Sunscreen SPF50 Broad Spectrum
NDC: 84616-002 | Form: CREAM
Manufacturer: SEORIN COMPANY Co., Ltd.
Category: otc | Type: HUMAN OTC DRUG LABEL
Date: 20240730

ACTIVE INGREDIENTS: ZINC OXIDE 17 g/100 mL
INACTIVE INGREDIENTS: POLYGLYCERYL-3 POLYDIMETHYLSILOXYETHYL DIMETHICONE (4000 MPA.S); ARTEMISIA ANNUA LEAF; HYALURONATE SODIUM; TRIETHOXYCAPRYLYLSILANE; CRYPTOMERIA JAPONICA LEAF; ASCORBIC ACID; WATER; PROPYLHEPTYL CAPRYLATE; DISTEARDIMONIUM HECTORITE; BUTYLENE GLYCOL; BUTYLOCTYL SALICYLATE; CYCLOMETHICONE 6; METHYL TRIMETHICONE; CAPRYLYL TRISILOXANE; 1,2-HEXANEDIOL; POLYGLYCERYL-2 DIPOLYHYDROXYSTEARATE; CAPRYLYL GLYCOL; ETHYLHEXYLGLYCERIN; PINE NEEDLE OIL (PINUS SYLVESTRIS); ISODODECANE; CHAMAEMELUM NOBILE FLOWER OIL; POLYMETHYLSILSESQUIOXANE (4.5 MICRONS); BETULA PLATYPHYLLA VAR. JAPONICA RESIN; GLYCERYL CAPRYLATE; NELUMBO NUCIFERA LEAF; SACCHAROMYCES CEREVISIAE; TOCOPHEROL; PROPANEDIOL; METHYL METHACRYLATE/GLYCOL DIMETHACRYLATE CROSSPOLYMER; MAGNESIUM SULFATE, UNSPECIFIED; GLYCERIN; GLYCERYL GLUCOSIDE; HYALURONIC ACID

Round Lab
Birch Juice
Mild-Up UVLOCK
Sunscreen
SPF50+ Broad Spectrum

Active Ingredients

Zinc Oxide 17%

Purpose

Sunscreen

Uses

- helps prevent sunburn
- if used as directed with other sun protection measures (see Directions) decreases the risk of skin cancer and early skin aging caused by the sun.

Warnings

For external use only.

Do not use on damaged or broken skin.

When using this product keep out of eyes. Rinse with water to remove

Stop use and ask a doctor if rash occurs

Keep out of reach of children.

If swallowed, get medical help or contact a Poison Control Center right away.

Directions

- apply liberally and evenly 15 minutes before sun exposure.
- Sun protection measures.

Spending time in the sun increases your risk of skin cancer and early aging. To decrease this risk, regularly use a sunscreen with a Broad Spectrum SPF value of 15 or higher and other sun protection measures including: limit time in the sun, especially from 10 a.m. - 2 p.m., wear long-sleeved shirts, pants, hats, and sunglasses

- children under 6 months of age: Ask a doctor
- reapply at least every 2 hours.
- use a water-resistant sunscreen if swimming or sweating

Other Information

- protect the product from excessive heat and direct sun

Inactive ingredients

Water, Cyclohexasiloxane, Butyloctyl Salicylate, Propanediol, Propylheptyl Caprylate, Isododecane, Caprylyl Methicone, Polyglycery-3 Polydimethylsiloxyethyl Dimethicone, Methyl Methacrylate Crosspolymer, Methyl Trimethicone, Disteardimonium Hectorite, Magnesium Sulfate, Triethoxycaprylysilane, 1,2-Hexanediol, Polyglyceryl-2 Dipolyhydroxystearate, Polymethylsilsesquioxane, Lauryl Polyglyceryl-3 Polydimethyisiloxyethyl Dimethicone, Butylene Glycol, Betula Platyphylla Japonica Juice, Glyceryl Caprylate, Caprylyl Glycol, Ethylhexy glycerin, Artemisia Ánnua Extract, Anthemis Nobilis Flower Oil, Sodium Hyaluronate, Pinus Sylvestris Leaf Oil, Glycerin, Nelumbo Nucifera Leaf Extract, Cryptomeria Japonica Leaf Extract, Saccharomyces Ferment Filtrate, Tocopherol, Glyceryl Glucoside, Hyaluronic Acid, Ascorbic Acid

Questions or comments?

www.roundlab.com

PACKAGE LABEL

BIRCH JUICE

MILD-UP UVLOCK

SUNSCREEN

SPF50+ Broad spectrum

ROUND LAB

50nL 1.69fl. oz.